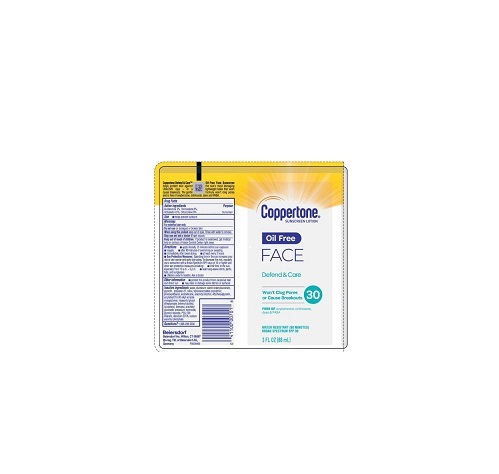 DRUG LABEL: Coppertone Oil Free Sunscreen SPF 30
NDC: 66800-3900 | Form: LOTION
Manufacturer: Beiersdorf Inc
Category: otc | Type: HUMAN OTC DRUG LABEL
Date: 20251231

ACTIVE INGREDIENTS: OCTOCRYLENE 6 g/100 g; AVOBENZONE 3 g/100 g; HOMOSALATE 8 g/100 g; OCTISALATE 4.5 g/100 g
INACTIVE INGREDIENTS: SILICON DIOXIDE; WATER; STYRENE/ACRYLAMIDE COPOLYMER (MW 500000); PHENOXYETHANOL; ARACHIDYL GLUCOSIDE; SYNTHETIC BEESWAX; POTASSIUM HYDROXIDE; PEG-100 STEARATE; GLYCERIN; ALUMINUM STARCH OCTENYLSUCCINATE; POLYESTER-7; ISODODECANE; ETHYLHEXYLGLYCERIN; NEOPENTYL GLYCOL DIHEPTANOATE; DOCOSANOL; TOCOPHEROL; GLYCERYL STEARATE SE; DISODIUM EDTA-COPPER; SODIUM ASCORBYL PHOSPHATE; ARACHIDYL ALCOHOL; CARBOMER INTERPOLYMER TYPE A (55000 CPS)

Oil Free Lotion SPF 30

Active ingredients

Avobenzone 3%, Homosalate 8%, Octisalate 4.5%, Octocrylene 6%

Purpose

Sunscreen

Uses

■ helps prevent sunburn

■ if used as directed with other sun protection measures (see Directions), decreases the risk of skin cancer and early skin aging caused by the sun

Warnings

For external use only

Do not useon damaged or broken skin

WHEN USING

When using this productkeep out of eyes. Rinse with water to remove.

Stop use and ask a doctor ifrash occurs

Keep out of reach of children.If product is swallowed, get medical help or contact a Poison Control Center right away.

Directions

■ apply liberally 15 minutes before sun exposure

■ reapply:

■ after 80 minutes of swimming or sweating

■ immediately after towel drying

■ at least every 2 hours

■ Sun Protection Measures.Spending time in the sun increases your risk of skin cancer and early skin aging. To decrease this risk, regularly use a sunscreen with a Broad Spectrum SPF value of 15 or higher and other sun protection measures including:

■ limit time in the sun, especially from 10 a.m. – 2 p.m.

■ wear long-sleeve shirts, pants, hats, and sunglasses

■ children under 6 months: Ask a doctor

Other information

■ protect this product from excessive heat and direct sun

■ may stain or damage some fabrics or surfaces

Inactive ingredients

water, aluminum starch octenylsuccinate, glycerin, polyester-27, silica, styrene/acrylates copolymer, phenoxyethanol, isododecane, arachidyl alcohol, ethylhexylglycerin, acrylates/C10-30 alkyl acrylate crosspolymer, neopentyl glycol diheptanoate, behenyl alcohol, tocopherol, beeswax, arachidyl glucoside, potassium hydroxide, glyceryl stearate, PEG-100 stearate, disodium EDTA, sodium ascorbyl phosphate

PACKAGE LABEL

Coppertone®Sunscreen Lotion

Oil Free Face

Defend & Care

30

Won't Clog Pores or Cause Breakouts

Free Of oxybenzone, octinoxate, dyes & PABA

Water Resistant (80 Minutes)

Broad Specturm SPF 30

3 FL OZ (88 mL)